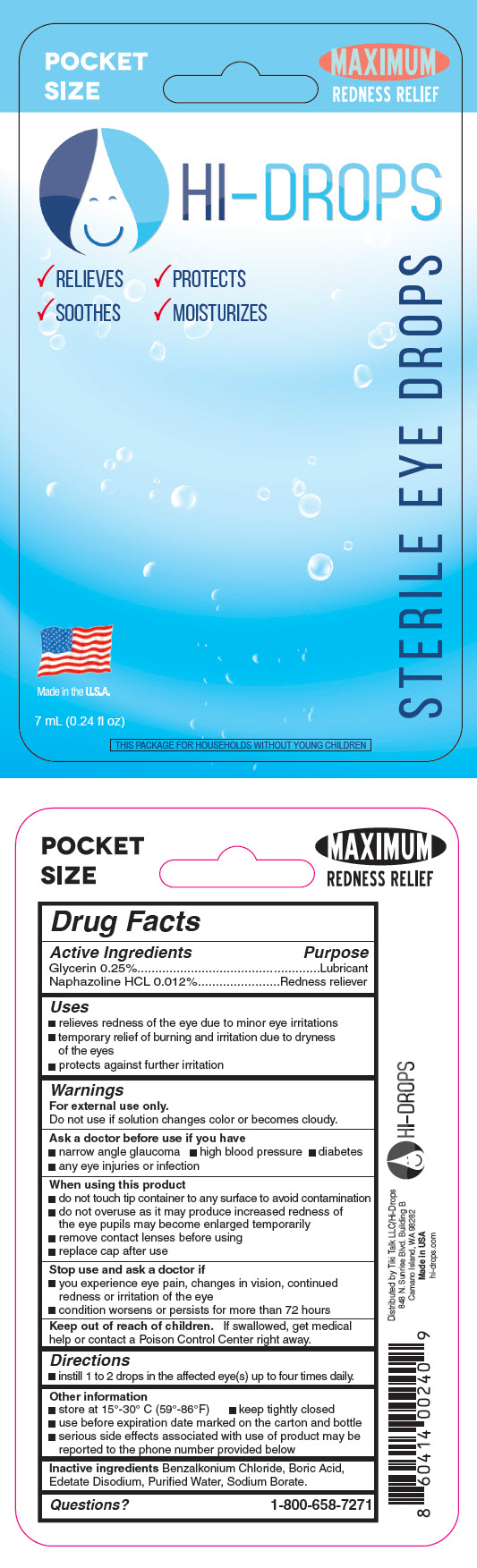 DRUG LABEL: Hi-Drops
NDC: 72254-123 | Form: SOLUTION/ DROPS
Manufacturer: Tiki Talk LLC/Hi-Drops
Category: otc | Type: HUMAN OTC DRUG LABEL
Date: 20210112

ACTIVE INGREDIENTS: Naphazoline Hydrochloride 0.1 mg/1 mL; Glycerin 2.5 mg/1 mL
INACTIVE INGREDIENTS: Benzalkonium Chloride; Boric Acid; Edetate Disodium; Water; Sodium Borate

Hi-Drops

Drug Facts

Active Ingredients | Purpose
Glycerin 0.25% | Lubricant
Naphazoline HCL 0.012% | Redness reliever

Uses

- relieves redness of the eye due to minor eye irritations
- temporary relief of burning and irritation due to dryness of the eyes
- protects against further irritation

Warnings

For external use only.

Do not use if solution changes color or becomes cloudy.

Ask a doctor before use if you have

- narrow angle glaucoma
- high blood pressure
- diabetes
- any eye injuries or infection

When using this product

- do not touch tip container to any surface to avoid contamination
- do not overuse as it may produce increased redness of the eye pupils may become enlarged temporarily
- remove contact lenses before using
- replace cap after use

Stop use and ask a doctor if

- you experience eye pain, changes in vision, continued redness or irritation of the eye
- condition worsens or persists for more than 72 hours

Keep out of reach of children. If swallowed, get medical help or contact a Poison Control Center right away.

Directions

- instill 1 to 2 drops in the affected eye(s) up to four times daily.

Other information

- store at 15°-30° C (59°-86°F)
- keep tightly closed
- use before expiration date marked on the carton and bottle
- serious side effects associated with use of product may be reported to the phone number provided below

Inactive ingredients

Benzalkonium Chloride, Boric Acid, Edetate Disodium, Purified Water, Sodium Borate.

Questions?

1-800-658-7271

Distributed by Tiki Talk LLC/Hi-Drops
848 N. Sunrise Blvd. Building B
Camano Island, WA 98282

PRINCIPAL DISPLAY PANEL - 7 mL Bottle Blister Pack

POCKET
SIZE

MAXIMUM
REDNESS RELIEF

HI–DROPS

✓RELIEVES ✓PROTECTS

✓SOOTHES ✓MOISTURIZES

Made in the U.S.A.

7 mL (0.24 fl oz)

THIS PACKAGE FOR HOUSEHOLDS WITHOUT YOUNG CHILDREN

STERILE EYE DROPS